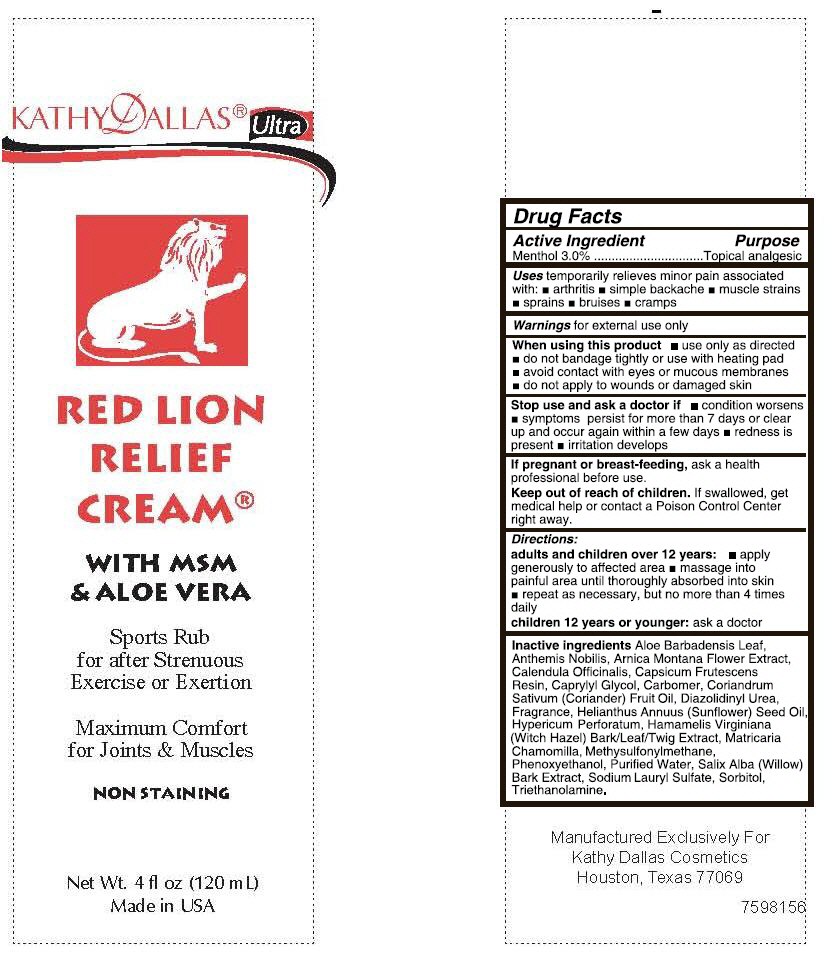 DRUG LABEL: Red Lion Relief
NDC: 58133-075 | Form: CREAM
Manufacturer: Cosmetic Specialty labs, Inc.
Category: otc | Type: HUMAN OTC DRUG LABEL
Date: 20140127

ACTIVE INGREDIENTS: menthol 3 g/100 g
INACTIVE INGREDIENTS: ALOE VERA LEAF; ARNICA MONTANA FLOWER; 1,3-BUTYLENE GLYCOL; CAPRYLYL GLYCOL; CARBOMER HOMOPOLYMER TYPE B (ALLYL SUCROSE CROSSLINKED); CETOSTEARYL ALCOHOL; CETYL ALCOHOL; ORANGE OIL; PALMAROSA OIL; EUCALYPTUS OIL; HAMAMELIS VIRGINIANA ROOT BARK/STEM BARK; LAVENDER OIL; MENTHA PIPERITA LEAF; DIMETHYL SULFONE; PHENOXYETHANOL; WATER; SALIX ALBA BARK; SORBITOL; .ALPHA.-TOCOPHEROL ACETATE; TROLAMINE

ACTIVE INGREDIENT

Menthol 3.0%

PURPOSE

Topical analgesic

USES

temporarily relieves minor pain associated with:

- arthritis
- simple backache
- muscle strains
- sprains
- bruises
- cramps

WARNINGS

for external use only

When using this product

- use only as directed
- do not bandage tightly or use with heating pad
- avoid contact with the eyes or mucous membranes
- do not apply to wounds or damaged skin

Stop use and ask a doctor if

- condition worsens
- symptoms perist for more than 7days or clear up and occur again within a few days
- redness is present
- irritation develops

If pregnant or breast-feeding

ask a health professional before use

KEEP OUT OF REACH OF CHILDREN

If swallowed, get medical help or contact a poison control center right away.

DIRECTIONS

Adults and children over 12 years

- apply generously to affected area
- massage into painful area until thoroughly absorbed into the skin
- repeat as necessary, no more than 4 times daily

Children 12 years or younger

ask a doctor

INACTIVE INGREDIENTS

Aloe Barbadensis Leaf, Arnica Montana Flower Extract, Butylene Glycol, Caprylyl Glycol, Carbomer, Cetearyl Alcohol, Cetyl Alcohol, Citrus Aurantium Dulcis (Orange) Peel Oil, Cymbopogon Martinii (Palmarosa) Oil, Eucalyptus Globulus Leaf Oil, Hamamelis Virginiana (Witch Hazel) Bark / Leaf / Twig Extract, Lavandula Angustifolia (Lavender) Oil, Mentha Piperita (Peppermint) Leaf Oil, Methylsulfonylmethane, Phenoxyethanol, Purified Water, Salix Alba (Willow) Bark Extract, Sorbitol, Tocopheryl Acetate, Triethanolamine.